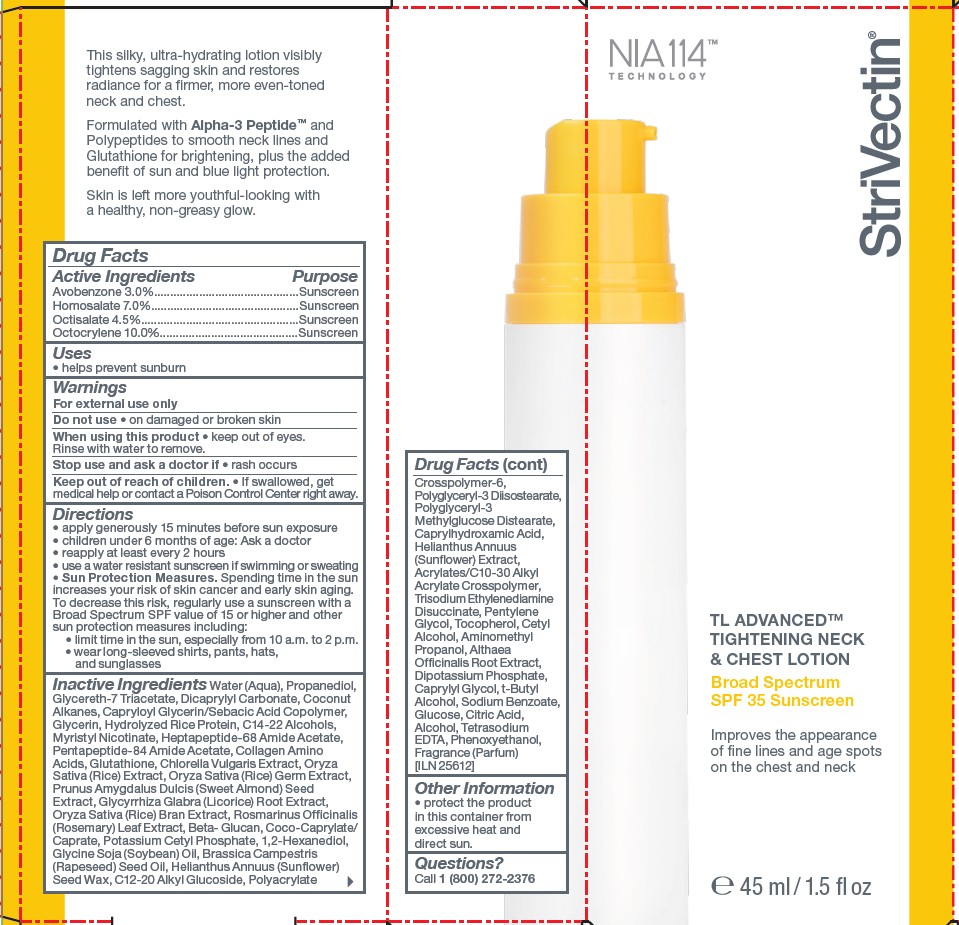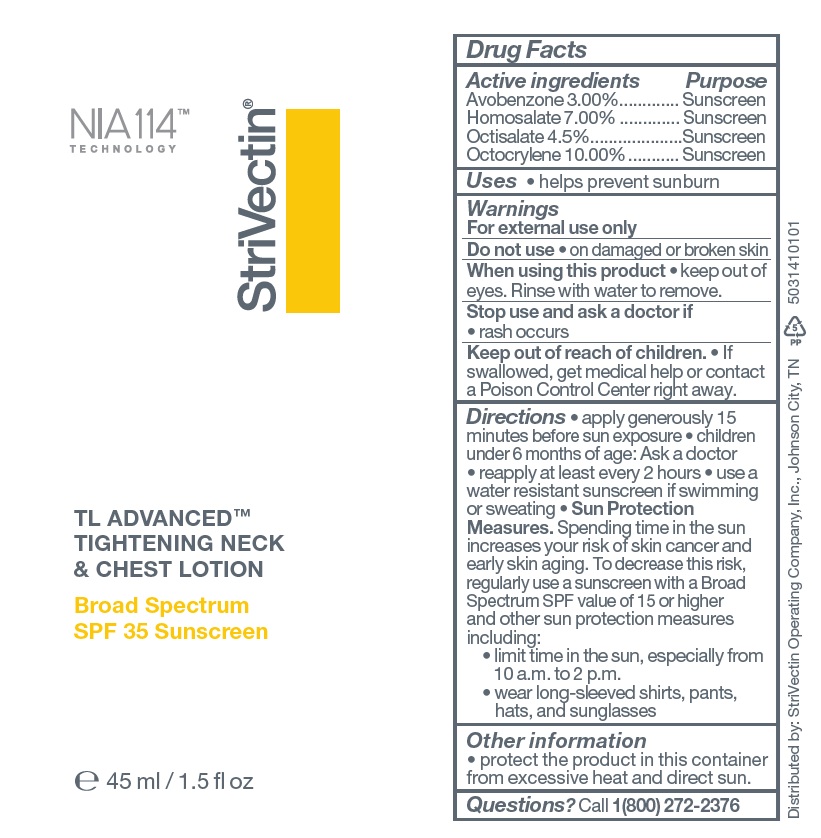 DRUG LABEL: StriVectin TL Advanced Tightening Neck and Chest Broad Spectrum SPF 35 Sunscreen
NDC: 76147-400 | Form: CREAM
Manufacturer: StriVectin Operating Company, Inc.
Category: otc | Type: HUMAN OTC DRUG LABEL
Date: 20260115

ACTIVE INGREDIENTS: AVOBENZONE 3 g/100 mL; OCTOCRYLENE 10 g/100 mL; HOMOSALATE 7 g/100 mL; OCTISALATE 4.5 g/100 mL
INACTIVE INGREDIENTS: COCONUT ALKANES; POLYACRYLATE CROSSPOLYMER-6; PRUNUS AMYGDALUS DULCIS (SWEET ALMOND) SEED; ALTHAEA OFFICINALIS ROOT; CAPRYLHYDROXAMIC ACID; 1,2-HEXANEDIOL; BRASSICA CAMPESTRIS (RAPESEED) SEED OIL; CHLORELLA VULGARIS; HYDROLYZED RICE PROTEIN (ENZYMATIC; 2000 MW); CITRIC ACID; YEAST .BETA.-D-GLUCAN; GLYCERETH-7 TRIACETATE; AMINO ACIDS, SOURCE UNSPECIFIED; WATER; CETYL ALCOHOL; PHENOXYETHANOL; DICAPRYLYL CARBONATE; PROPANEDIOL; POLYGLYCERYL-3 METHYLGLUCOSE DISTEARATE; RICE GERM; ALCOHOL; TOCOPHEROL; POTASSIUM PHOSPHATE, DIBASIC; GLUTATHIONE; TRISODIUM ETHYLENEDIAMINE DISUCCINATE; SODIUM BENZOATE; T-BUTYL ALCOHOL; GLUCOSE; CAPRYLYL GLYCOL; GLYCYRRHIZA GLABRA (LICORICE) ROOT; ORYZA SATIVA (RICE) BRAN; C12-20 ALKYL GLUCOSIDE; CAPRYLOYL GLYCERIN/SEBACIC ACID COPOLYMER (2000 MPA.S); MYRISTYL NICOTINATE; PENTYLENE GLYCOL; ROSMARINUS OFFICINALIS (ROSEMARY) LEAF OIL; GLYCERIN; POTASSIUM CETYL PHOSPHATE; HELIANTHUS ANNUUS (SUNFLOWER) SEED; C14-22 ALCOHOLS; COCO-CAPRYLATE/CAPRATE; ACRYLATES/C10-30 ALKYL ACRYLATE CROSSPOLYMER (60000 MPA.S); TETRASODIUM EDTA; GLYCINE SOJA (SOYBEAN) OIL UNSAPONIFIABLES; HELIANTHUS ANNUUS (SUNFLOWER) SEED WAX; POLYGLYCERYL-3 DIISOSTEARATE; AMINOMETHYL PROPANOL

StriVectin TL Advanced Tightening Neck and Chest Lotion Broad Spectrum SPF 35 Sunscreen

Active Ingredients

Avobenzone 3.0%
Homosalate 7.0%
Octisalate 4.5%
Octocrylene 10.0%

Purpose

Sunscreen

Uses

- helps prevent sunburn

Warnings

For external use only

Do not use

- on damaged or broken skin

When using this product

- keep out of eyes. Rinse with water to remove.

Stop use and ask a doctor if

- rash occurs

Keep out of reach of children.

- If swallowed, get medical help or contact a Poison Control Center right away.

Directions

- apply generously 15 minutes before sun exposure
- children under 6 months of age: Ask a doctor
- reapply at least every 2 hours
- use a water resistant sunscreen if swimming or sweating
- Sun Protection Measures. Spending time in the sun increases your risk of skin cancer and early skin aging. To decrease this risk, regularly use a sunscreen with a Broad Spectrum SPF value of 15 or higher and other sun protection measures including:
- limit time in the sun, especially from 10 a.m. to 2 p.m.
- wear long-sleeved shirts, pants, hats, and sunglasses

Inactive Ingredients

Water (Aqua), Propanediol, Glycereth-7 Triacetate, Dicaprylyl Carbonate, Coconut Alkanes, Capryloyl Glycerin/Sebacic Acid Copolymer, Glycerin, Hydrolyzed Rice Protein, C14-22 Alcohols, Myristyl Nicotinate, Heptapeptide-68 Amide Acetate, Pentapeptide-84 Amide Acetate, Collagen Amino Acids, Glutathione, Chlorella Vulgaris Extract, Oryza Sativa (Rice) Extract, Oryza Sativa (Rice) Germ Extract, Prunus Amygdalus Dulcis (Sweet Almond) Seed Extract, Glycyrrhiza Glabra (Licorice) Root Extract, Oryza Sativa (Rice) Bran Extract, Rosmarinus Officinalis (Rosemary) Leaf Extract, Beta-Glucan, Coco-Caprylate/Caprate, Potassium Cetyl Phosphate, 1,2-Hexanediol, Glycine Soja (Soybean) Oil, Brassica Campestris (Rapeseed) Seed Oil, Helianthus Annuus (Sunflower) Seed Wax, C12-20 Alkyl Glucoside, Polyacrylate Crosspolymer-6, Polyglyceryl-3 Diisostearate, Polyglyceryl-3 Methylglucose Distearate, Caprylhydroxamic Acid, Helianthus Annuus (Sunflower) Extract, Acrylates/C10-30 Alkyl Acrylate Crosspolymer, Trisodium Ethylenediamine Disuccinate, Pentylene Glycol, Tocopherol, Cetyl Alcohol, Aminomethyl Propanol, Althaea Officinalis Root Extract, Dipotassium Phosphate, Caprylyl Glycol, t-Butyl Alcohol, Sodium Benzoate, Glucose, Citric Acid, Alcohol, Tetrasodium EDTA, Phenoxyethanol, Fragrance (Parfum) [ILN 25612]

Other Information

- protect the product in this container from excessive heat and direct sun.

Questions?

Call 1 (800) 272-2376

PDP Tube

StriVectin

TL Advanced Tightening Neck & Chest Lotion

Broad Spectrum SPF 35 Sunscreen

45 ml / 1.5 oz

Distributed by: StriVectin Operating Company, Inc., Johnson City, TN

5031410101

PDP Carton

StriVectin

TL Advanced Tightening Neck & Chest Lotion

Broad Spectrum SPF 35 Sunscreen

45 ml / 1.5 oz

Distributed by: StriVectin Operating Company, Inc., Johnson City, TN

5031413401